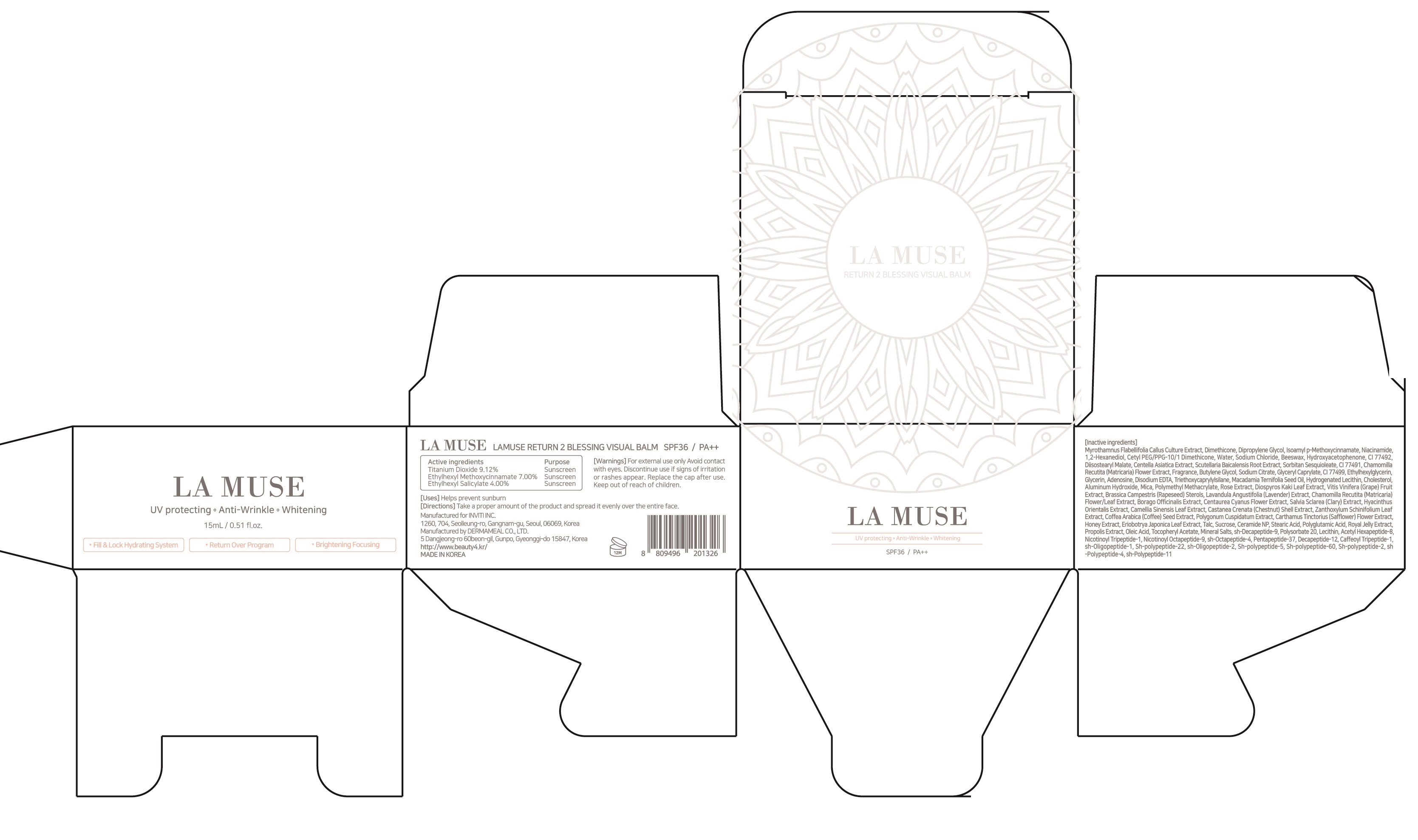 DRUG LABEL: Lamuse Return 2 Blessing Visual Balm
NDC: 72161-010 | Form: CREAM
Manufacturer: INVITI INC.
Category: otc | Type: HUMAN OTC DRUG LABEL
Date: 20180315

ACTIVE INGREDIENTS: Titanium Dioxide 1.36 g/15 mL; Octinoxate 1.05 g/15 mL; Octisalate 0.60 g/15 mL
INACTIVE INGREDIENTS: Dimethicone; Dipropylene Glycol

ACTIVE INGREDIENT

Active ingredients: Titanium Dioxide 9.12%, Ethylhexyl Methoxycinnamate 7.00%, Ethylhexyl Salicylate 4.00%

INACTIVE INGREDIENT

Inactive Ingredients:
Inactive ingredients: Myrothamnus Flabellifolia Callus Culture Extract, Dimethicone, Dipropylene Glycol, Isoamyl p-Methoxycinnamate, Niacinamide, 1,2-Hexanediol, Cetyl PEG/PPG-10/1 Dimethicone, Water, Sodium Chloride, Beeswax, Hydroxyacetophenone, CI 77492, Diisostearyl Malate, Centella Asiatica Extract, Scutellaria Baicalensis Root Extract, Sorbitan Sesquioleate, CI 77491, Chamomilla Recutita (Matricaria) Flower Extract, Fragrance, Butylene Glycol, Sodium Citrate, Glyceryl Caprylate, CI 77499, Ethylhexylglycerin, Glycerin, Adenosine, Disodium EDTA, Triethoxycaprylylsilane, Macadamia Ternifolia Seed Oil, Hydrogenated Lecithin, Cholesterol, Aluminum Hydroxide, Mica, Polymethyl Methacrylate, Rose Extract, Diospyros Kaki Leaf Extract, Vitis Vinifera (Grape) Fruit Extract, Brassica Campestris (Rapeseed) Sterols, Lavandula Angustifolia (Lavender) Extract, Chamomilla Recutita (Matricaria) Flower/Leaf Extract, Borago Officinalis Extract, Centaurea Cyanus Flower Extract, Salvia Sclarea (Clary) Extract, Hyacinthus Orientalis Extract, Camellia Sinensis Leaf Extract, Castanea Crenata (Chestnut) Shell Extract, Zanthoxylum Schinifolium Leaf Extract, Coffea Arabica (Coffee) Seed Extract, Polygonum Cuspidatum Extract, Carthamus Tinctorius (Safflower) Flower Extract, Honey Extract, Eriobotrya Japonica Leaf Extract, Talc, Sucrose, Ceramide NP, Stearic Acid, Polyglutamic Acid, Royal Jelly Extract, Propolis Extract, Oleic Acid, Tocopheryl Acetate, Mineral Salts, sh-Decapeptide-9, Polysorbate 20, Lecithin, Acetyl Hexapeptide-8, Nicotinoyl Tripeptide-1, Nicotinoyl Octapeptide-9, sh-Octapeptide-4, Pentapeptide-37, Decapeptide-12, Caffeoyl Tripeptide-1, sh-Oligopeptide-1, Sh-polypeptide-22, sh-Oligopeptide-2, Sh-polypeptide-5, Sh-polypeptide-60, Sh-polypeptide-2, sh-Polypeptide-4, sh-Polypeptide-11

PURPOSE

Purpose: Sunscreen

WARNINGS

For external use only

Avoid contact with eyes.

Discontinue use if signs of irritation or rashes appear.

Replace the cap after use.

Keep out of reach of children.

DESCRIPTION

Uses:

Helps prevent sunburn

Directions:

Take a proper amount of the product and spread it evenly over the entire face.